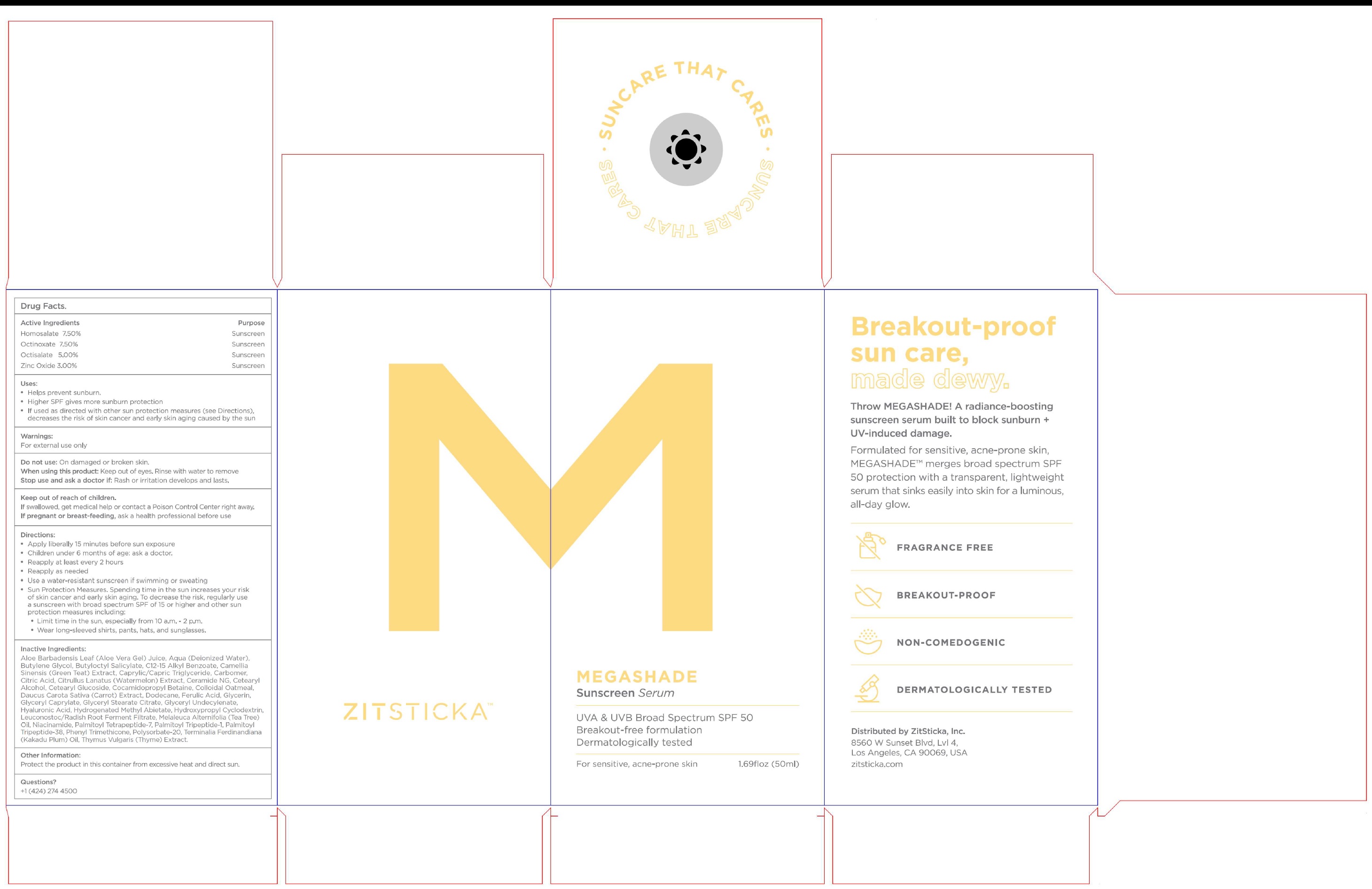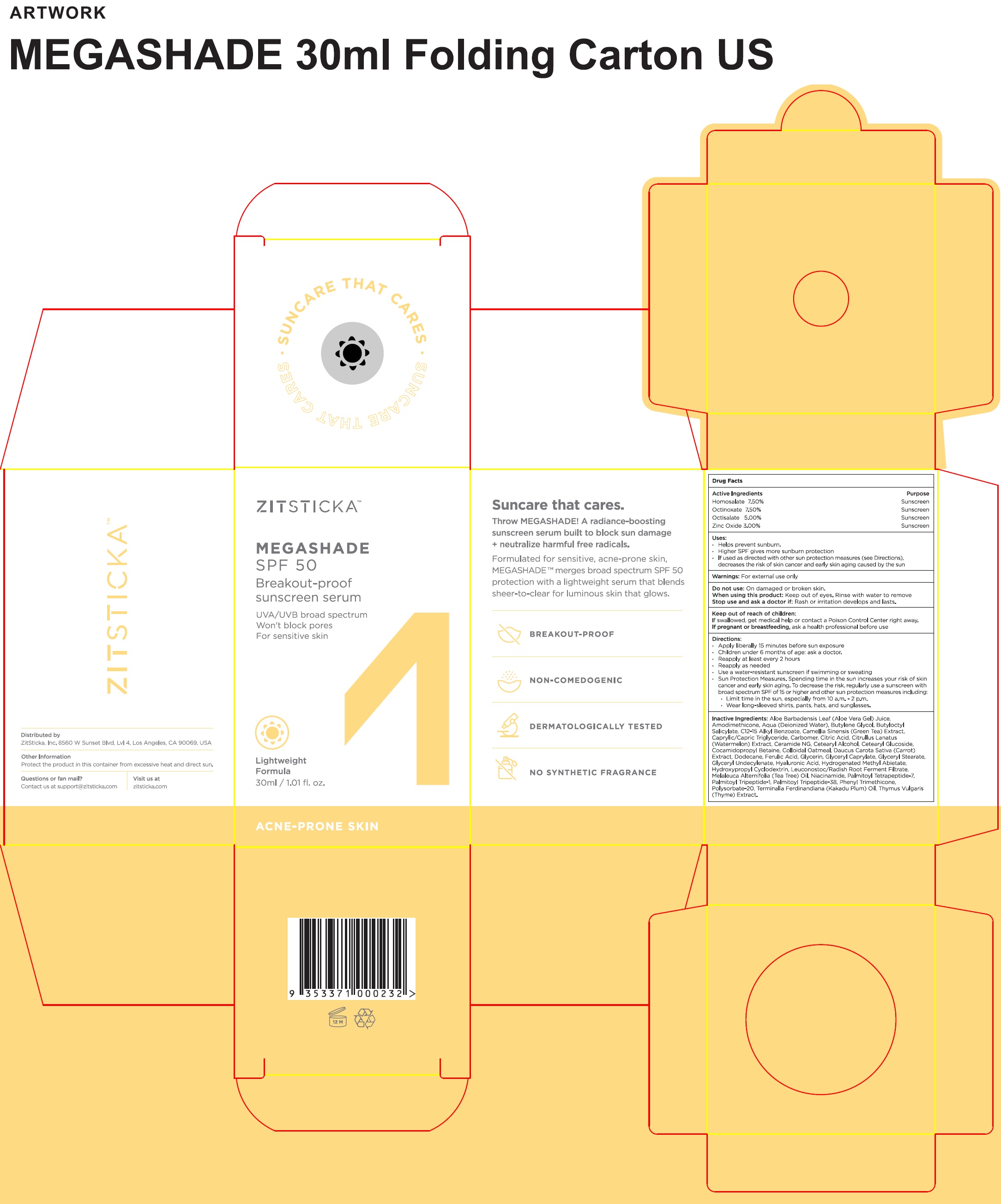 DRUG LABEL: ZITSTICKA MEGASHADE SUNSCREEN SERUM (SPF-50)
NDC: 81746-183 | Form: LIQUID
Manufacturer: ZITSTICKA, Inc
Category: otc | Type: HUMAN OTC DRUG LABEL
Date: 20231111

ACTIVE INGREDIENTS: HOMOSALATE 75 mg/1 mL; OCTINOXATE 75 mg/1 mL; OCTISALATE 50 mg/1 mL; ZINC OXIDE 30 mg/1 mL
INACTIVE INGREDIENTS: ALOE VERA LEAF; WATER; BUTYLENE GLYCOL; BUTYLOCTYL SALICYLATE; ALKYL (C12-15) BENZOATE; GREEN TEA LEAF; MEDIUM-CHAIN TRIGLYCERIDES; CARBOMER HOMOPOLYMER, UNSPECIFIED TYPE; CITRIC ACID MONOHYDRATE; WATERMELON; CERAMIDE NG; CETOSTEARYL ALCOHOL; CETEARYL GLUCOSIDE; COCAMIDOPROPYL BETAINE; OATMEAL; CARROT; DODECANE; FERULIC ACID; GLYCERIN; GLYCERYL CAPRYLATE; GLYCERYL STEARATE CITRATE; GLYCERYL 1-UNDECYLENATE; HYALURONIC ACID; HYDROGENATED METHYL ABIETATE; LEUCONOSTOC/RADISH ROOT FERMENT FILTRATE; MELALEUCA ALTERNIFOLIA LEAF; NIACINAMIDE; PALMITOYL TETRAPEPTIDE-7; PALMITOYL TRIPEPTIDE-1; PALMITOYL LYSYLDIOXYMETHIONYLLYSINE; PHENYL TRIMETHICONE; POLYSORBATE 20; KAKADU PLUM; THYME

ZITSTICKA MEGASHADE SUNSCREEN SERUM (SPF-50)

Active Ingredients

Homosalate 7.50% Octinoxate 7.50% Octisalate 5.00% Zinc Oxide 3.00%

Purpose

Sunscreen

Uses:

- Helps prevent sunburn.
- Higher SPF gives more sunburn protection
- If used as directed with other sun protection measures (see Directions), decreases the risk of skin cancer and early skin aging caused by the sun

Warnings:

For external use only

Do not use:

On damaged or broken skin.

When using this product:

Keep out of eyes. Rinse with water to remove

Stop use and ask a doctor if:

Rash or irritation develops and lasts.

Keep out of reach of children.

If swallowed, get medical help or contact a Poison Control Center right away.

If pregnant or breast-feeding,

ask a health professional before use

Directions:

• Apply liberally 15 minutes before sun exposure • Children under 6 months of age: ask a doctor. • Reapply at least every 2 hours • Reapply as needed • Use a water-resistant sunscreen if swimming or sweating • Sun Protection Measures. Spending time in the sun increases your risk of skin cancer and early skin aging. To decrease the risk, regularly use a sunscreen with broad spectrum SPF of 15 or higher and other sun protection measures including: • Limit time in the sun, especially from 10 a.m. - 2 p.m. • Wear long-sleeved shirts, pants, hats, and sunglasses.

Inactive Ingredients:

Aloe Barbadensis Leaf (Aloe Vera Gel) Juice, Aqua (Deionized Water), Butylene Glycol, Butyloctyl Salicylate, C12-15 Alkyl Benzoate, Camellia Sinensis (Green Teat) Extract, Caprylic/Capric Triglyceride, Carbomer, Citric Acid, Citrullus Lantus (Watermelon) Extract, Ceramide NG, Cetearyl Alcohol, Cetearyl Glucoside, Cocamidopropyl Betaine, Colloidal Oatmeal, Daucus Carota Sativa (Carrot) Extract, Dodecane, Ferulic Acid, Glycerin, Glyceryl Caprylate, Glyceryl Stearate Citrate, Glyceryl Undecylenate, Hyaluronic Acid, Hydrogenated Methyl Abietate, Hydropropyl Cyclodextrin, Leuconostoc/Radish Root Ferment Filtrate, Melaleuca Alternifolia (Tea Tree) Oil, Niacinamide, Palmitoyl Tetrapeptide-7, Palmitoyl Tripeptide-1, Palmitoyl Tripeptide-38, Phenyl Trimethicone, Polysorbate-20, Terminalia Ferdinandiana (Kakadu Plum) Oil, Thymus Vulgaris (Thyme) Extract.

Other Information:

Protect the product in this container from excessive heat and direct sun.

Questions?

+1 (424) 274 4500